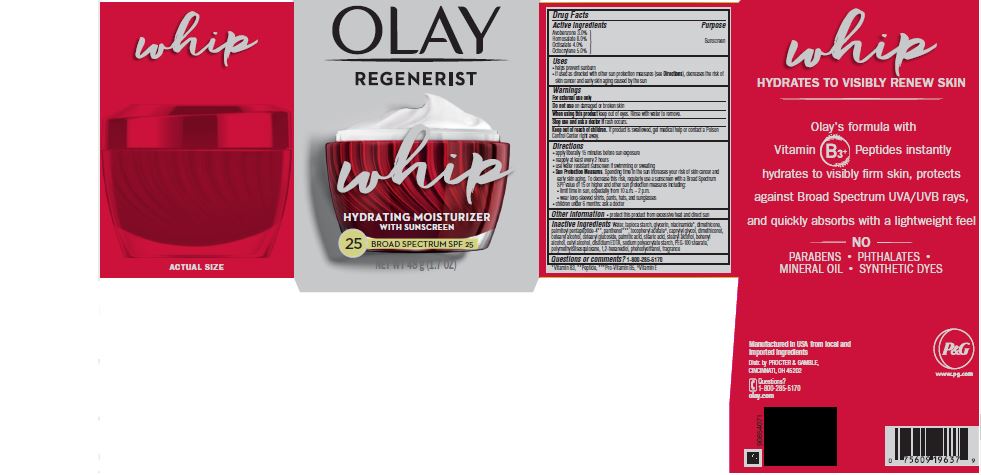 DRUG LABEL: Olay Regenerist Whip Moisturizer Broad Spectrum SPF 25 Sunscreen
NDC: 69423-466 | Form: CREAM
Manufacturer: The Procter & Gamble Manufacturing Company
Category: otc | Type: HUMAN OTC DRUG LABEL
Date: 20260226

ACTIVE INGREDIENTS: AVOBENZONE 3 g/100 g; HOMOSALATE 8 g/100 g; OCTISALATE 4 g/100 g; OCTOCRYLENE 5 g/100 g
INACTIVE INGREDIENTS: STARCH, TAPIOCA; ALPHA-TOCOPHEROL ACETATE; STEARYL ALCOHOL; CAPRYLYL GLYCOL; 1,2-HEXANEDIOL; DIMETHICONE; WATER; GLYCERIN; NIACINAMIDE; DIMETHICONOL GUM; PANTHENOL; PALMITOYL PENTAPEPTIDE-4; CETEARYL GLUCOSIDE; PEG-100 STEARATE; DOCOSANOL; CETYL ALCOHOL; EDETATE DISODIUM; CETOSTEARYL ALCOHOL; STEARIC ACID; PALMITIC ACID; POLYMETHYLSILSESQUIOXANE (4.5 MICRONS); PHENOXYETHANOL

Olay® Regnerist Whip Moisturizer with Sunscreen SPF 25
Broad Spectrum SPF 30

Drug Facts

ACTIVE INGREDIENT

Active ingredients | Purpose
Avobenzone 3.0% | Sunscreen
Homosalate 8.0% | Sunscreen
Octisalate 4.0% | Sunscreen
Octocrylene 5.0% | Sunscreen

Uses

- helps prevent sunburn
- if used as directed with other sun protection measures (see Directions), decreases the risk of skin cancer and early skin aging caused by the sun

Warnings

For external use only

Do not use on damaged or broken skin

When using this product keep out of eyes. Rinse with water to remove.

Stop use and ask a doctor if rash occurs

Keep out of reach of children. If product is swallowed, get medical help or contact a Poison Control Center right away.

Directions

- apply liberally 15 minutes before sun exposure
- reapply at least every 2 hours
- use water resistant sunscreen if swimming or sweating
- Sun Protection Measures. Spending time in the sun increases your risk of skin cancer and early skin aging. To decrease this risk, regularly use a sunscreen with a Broad Spectrum SPF value of 15 or higher and other sun protection measures including:
  - limit time in sun, especially from 10 a.m. – 2 p.m.
  - wear long-sleeved shirts, pants, hats, and sunglasses
- children under 6 months: ask a doctor

Other information

- protect this product from excessive heat and direct sun

Inactive ingredients

Water, tapioca starch, glycerin, niacinamide, dimethicone, palmitoyl pentapeptide-4, panthenol, tocopheryl acetate, caprylyl glycol, dimethiconol, cetearyl alcohol, cetearyl glucoside, palmitic acid, stearic acid, stearyl alcohol, behenyl alcohol, cetyl alcohol, disodium EDTA, sodium polyacrylate starch, PEG-100 stearate, polymethylsilsesquioxane, 1,2-hexanediol, phenoxyethanol, fragrance

Questions or comments?

Call 1-800-285-5170

Distr. by PROCTER & GAMBLE,
CINCINNATI, OH 45202

PRINCIPAL DISPLAY PANEL - 48 g Jar Carton

OLAY

REGENERIST WHIP

whip

HYDRATING MOISTURIZER

WITH SUNSCREEN
25

BROAD SPECTRUM SPF 25

NET WT 48 g (1.7 oz)